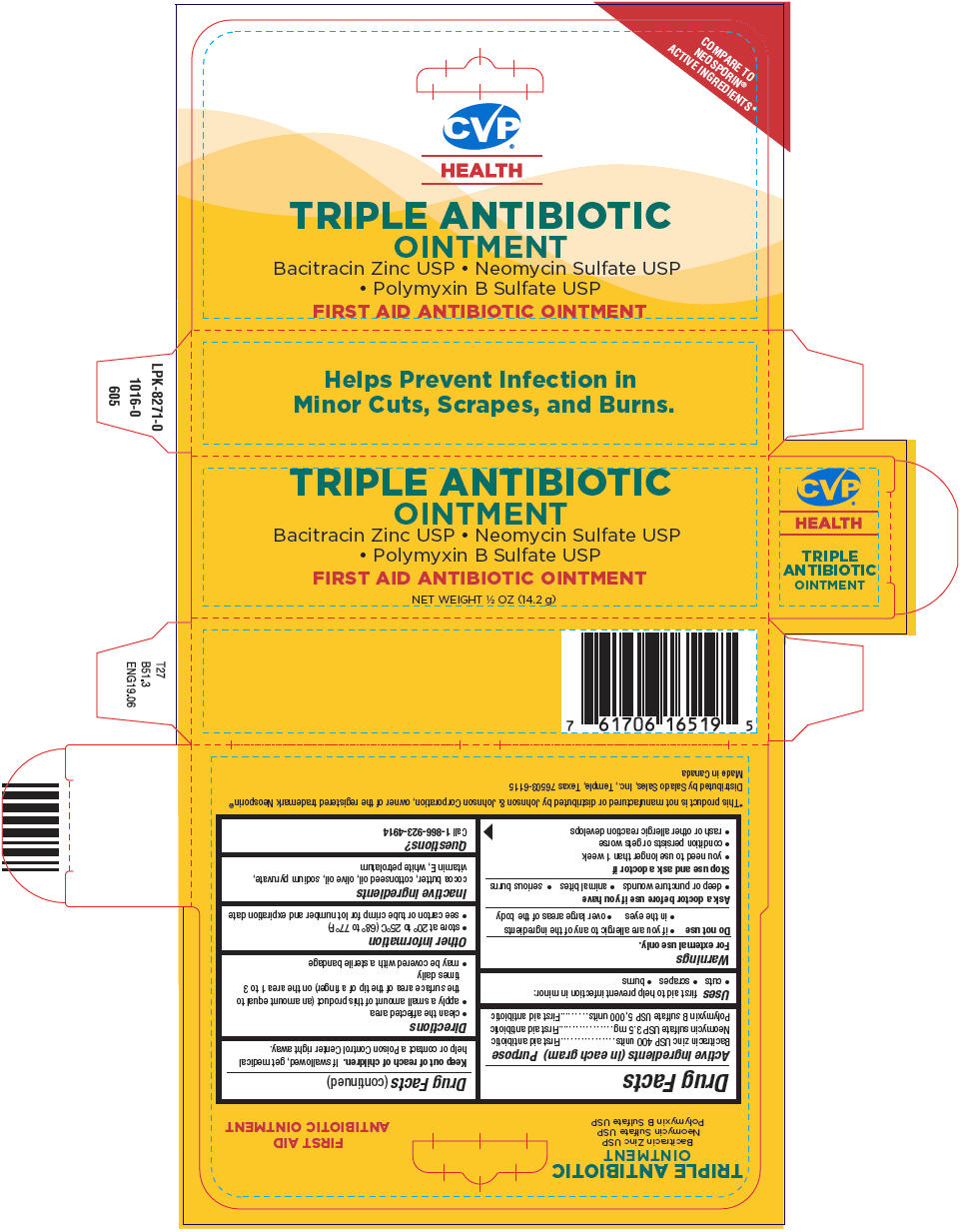 DRUG LABEL: Triple Antibiotic
NDC: 57243-120 | Form: OINTMENT
Manufacturer: Salado Sales, Inc
Category: otc | Type: HUMAN OTC DRUG LABEL
Date: 20250806

ACTIVE INGREDIENTS: BACITRACIN ZINC 400 [iU]/1 g; NEOMYCIN SULFATE 3.5 mg/1 g; POLYMYXIN B SULFATE 5000 [iU]/1 g
INACTIVE INGREDIENTS: SUCROSE; COTTONSEED OIL; OLIVE OIL; SODIUM PYRUVATE; .ALPHA.-TOCOPHEROL; PETROLATUM

Triple Antibiotic

Drug Facts

ACTIVE INGREDIENT

Active ingredients (in each gram) | Purpose
Bacitracin zinc USP 400 units | First aid antibiotic
Neomycin sulfate USP 3.5 mg | First aid antibiotic
Polymyxin B sulfate USP 5,000 units | First aid antibiotic

Uses

first aid to help prevent infection in minor:

- cuts
- scrapes
- burns

Warnings

For external use only.

Do not use

- if you are allergic to any of the ingredients
- in the eyes
- over large areas of the body

Ask a doctor before use if you have

- deep or puncture wounds
- animal bites
- serious burns

Stop use and ask a doctor if

- you need to use longer than 1 week
- condition persists or gets worse
- rash or other allergic reaction develops

Keep out of reach of children.If swallowed, get medical help or contact a Poison Control Center right away.

Directions

- clean the affected area
- apply a small amount of this product (an amount equal to the surface area of the tip of a finger) on the area 1 to 3 times daily
- may be covered with a sterile bandage

Other information

- store at 20° to 25°C (68° to 77°F)
- see carton or tube crimp for lot number and expiration date

Inactive ingredients

cocoa butter, cottonseed oil, olive oil, sodium pyruvate, vitamin E, white petrolatum

Questions?

Call 1-866-923-4914

Distributed by Salado Sales, Inc., Temple, Texas 76503-6115

PRINCIPAL DISPLAY PANEL - 14.2 g Tube Carton

TRIPLE ANTIBIOTIC
OINTMENT

Bacitracin Zinc USP • Neomycin Sulfate USP
• Polymyxin B Sulfate USP

FIRST AID ANTIBIOTIC OINTMENT

NET WEIGHT ½ OZ (14.2 g)